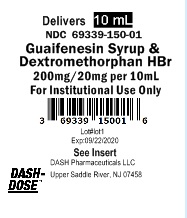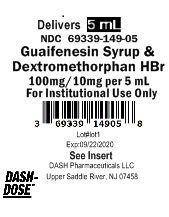 DRUG LABEL: Guaifenesin Syrup and Dextromethorphan
NDC: 69339-149 | Form: SYRUP
Manufacturer: Natco Pharma USA LLC
Category: otc | Type: HUMAN OTC DRUG LABEL
Date: 20231101

ACTIVE INGREDIENTS: GUAIFENESIN 100 mg/5 mL; DEXTROMETHORPHAN HYDROBROMIDE 10 mg/5 mL
INACTIVE INGREDIENTS: ANHYDROUS CITRIC ACID; DEXTROSE; FD&C RED NO. 40; MENTHOL; GLYCERIN; HIGH FRUCTOSE CORN SYRUP; WATER; SACCHARIN SODIUM; SODIUM BENZOATE

Guaifenesin Syrup and Dextromethorphan

PURPOSE

Non-Narcotic - Alcohol Free

DRUG FACTS

Active Ingredient (in each 5 mL cup) Purpose
Guaifenesin, USP 100mg .............................................................................................................................. Expectorant
Dextromethorphan HBr, USP 10mg ...................................................................................................... Cough Suppressant

Active Ingredient (in each 10 mL cup) Purpose
Guaifenesin, USP 200mg .............................................................................................................................. Expectorant
Dextromethorphan HBr, USP 20mg .......................................................................................................Cough Suppressant

Inactive Ingredients

Anhydrous citric acid, dextrose, FD&C Red No. 40, flavor, glycerin, high fructose corn syrup, menthol, purified water, saccharin sodium, sodium benzoate.

Uses

• helps loosen phlegm (mucus) and thin bronchial secretions to make coughs more productive.
• temporarily relieves cough due to minor throat and bronchial irritation as may occur with a cold.

Warnings

Do not use if you are now taking a prescription monoamine oxidase inhibitor (MAOI) or for two weeks after stopping the MAOI drug.

Ask a doctor before use if you have

• cough that occurs with too much phlegm (mucus)
• cough that lasts or is chronic such as occurs with smoking, asthma, chronic bronchitis or emphysema

Ask a doctor or pharmacist before use if you are taking any other drug

Stop use and ask a doctor if

• your cough lasts more than 7 days, comes back, or is accompanied by fever, rash, or persistant headache.
• you are hypersensitive to any of the ingredients

PREGNANCY OR BREAST FEEDING

If pregnant or breast-feeding, ask a health professional before use

Keep out of reach of children. In case of overdose, get medical help or contact a Poison Control Center right away (1-800-222-1222)

DIRECTIONS:

Age | Dose
Adults and children 12 years and over | 10 mL every 4 hours; Max dose is 60mL in 24-hours
Children under 12 years of age | Ask a doctor

HOW SUPPLIED:

Each 5 mL of Guaifenesin Syrup and Dextromethorphan contains Guaifenesin 100mg and Dextromethorphan Hydrobromide 10mg and is supplied in the following oral dosage forms:

NDC 69339-149-05 (1) unit dose cup 5mL
NDC 69339-149-19 100 (10x10) unit dose cups 5mL

Each 10 mL of Guaifenesin Syrup and Dextromethorphan
contains Guaifenesin 200mg and Dextromethorphan
Hydrobromide 20mg and is supplied in the following oral
dosage forms:

NDC 69339-150-01 (1) unit dose cup 10mL
NDC 69339-150-19 100 (10x10) unit dose cups 10mL

Other Information
• Store at controlled room temperature 20-25ºC (68-77ºF)
• Do not refrigerate
• Keep tightly closed
• Each 5mL contains sodium 3mg
• Each 10mL contains sodium 6mg
• Fruit punch flavor
• Do not use if lid seal is open or damaged
• See top of cup for lot number and expiration date

Questions or comments?
Call 201-786-6500

Dash Pharmaceuticals LLC
Upper Saddle River, NJ 07458

DP-UD-PI-AT-[117893] Rev 08/20

PRINCIPAL DISPLAY PANEL - 5 mL Unit Dose Cup Label

Delivers 5 mL
NDC 69339-149-05

GUAIFENESIN SYRUP &

DEXTROMETHORPHAN HBr

100 mg/10 mg per 5 mL

For Institutional Use Only

3 69339 14905 8

Lot # 111

Exp: 09/22/2020

See Insert

Dash Pharmaceuticals LLC

Upper Saddle River, NJ 07458

DASH-

DOSE

PRINCIPAL DISPLAY PANEL - 10 mL Unit Dose Cup Label

Delivers 10 mL
NDC 69339-150-01

GUAIFENESIN SYRUP &

DEXTROMETHORPHAN HBr

200 mg/20 mg per 10 mL

For Institutional Use Only

3 69339 15001 6

Lot # 111

Exp: 09/22/2020

See Insert

Dash Pharmaceuticals LLC

Upper Saddle River, NJ 07458

DASH-

DOSE